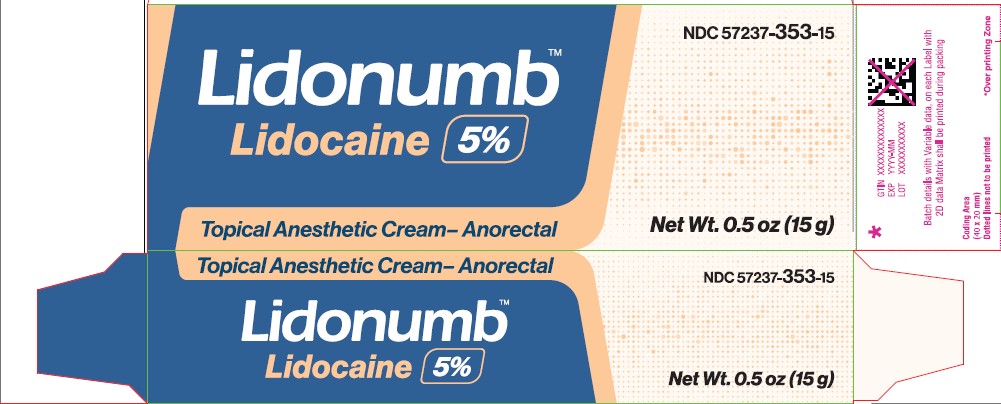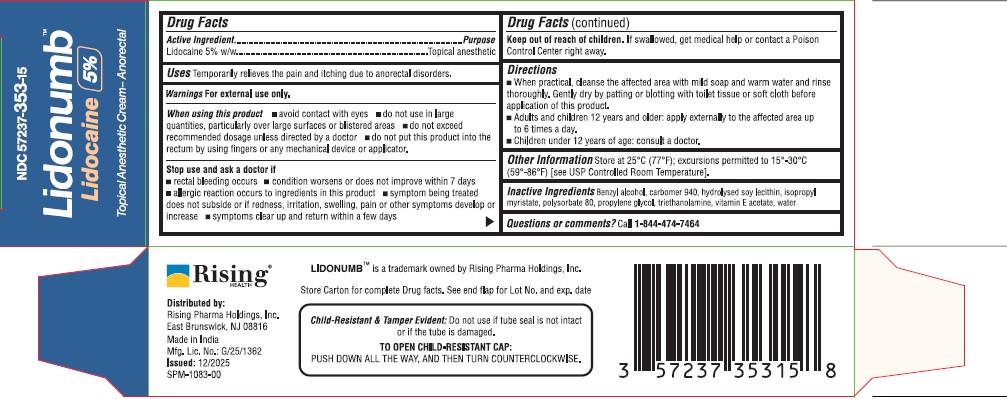 DRUG LABEL: Lidonumb
NDC: 57237-353 | Form: CREAM
Manufacturer: Rising Pharma Holdings, Inc.
Category: otc | Type: HUMAN OTC DRUG LABEL
Date: 20251216

ACTIVE INGREDIENTS: LIDOCAINE 0.05 g/1 g
INACTIVE INGREDIENTS: BENZYL ALCOHOL; CARBOMER 940; HYDROGENATED SOYBEAN LECITHIN; ISOPROPYL MYRISTATE; POLYSORBATE 80; PROPYLENE GLYCOL; TRIETHANOLAMINE; .ALPHA.-TOCOPHEROL; WATER

Lidonumb
Lidocaine 5%
Topical Anesthetic Cream- Anorectal

Active Ingredient

Lidocaine 5% w/w

Purpose

Topical anesthetic

Uses

Temporarily relieves the pain and itching due to anorectal disorders.

Warnings

For external use only.

When using this product

- avoid contact with eyes
- do not use in large quantities, particularly over large surfaces or blistered areas
- do not exceed recommended dosage unless directed by a doctor
- do not put this product into the rectum by using fingers or any mechnical device or applicator.

Stop use and ask a doctor if

- rectal bleeding occurs
- condition worsens or does not improve within 7 days
- allergic reaction occurs to ingredients in this product
- symptom being treated does not subside or if redness, irritation, swelling, pain or other symptoms develop or increase
- symptoms clear up and return within a few days

Keep out of reach of children.

If swallowed, get medical help or contact a Poison Control Center right away.

Directions

- When practical, cleanse the affected area with mild soap and warm water and rinse thoroughly. Gently dry by patting or blotting with toilet tissue or soft cloth before application of this product.
- Adults and children 12 years and older: apply externally to the affected area up to 6 times a day.
- Children under 12 years of age: consult a doctor.

Other Information

Store at 25°C (77°F); excursions permitted to 15°-30°C (59°-86°F) [see USP Controlled Room Temperature].

Inactive Ingredients

Benzyl alcohol, carbomer 940, hydrolysed soy lecithin, isopropyl myristate, polysorbate 80, propylene glycol, triethanolamine, vitamin E acetate, water

Questions or comments?

Call 1-844-474-7464

PACKAGE LABEL

Distributed by:

Rising Pharma Holdings, Inc.

East Brunswick, NJ 08816

Made in India

Mfg. lic. No.: G/25/1362

Issued: 12/2025